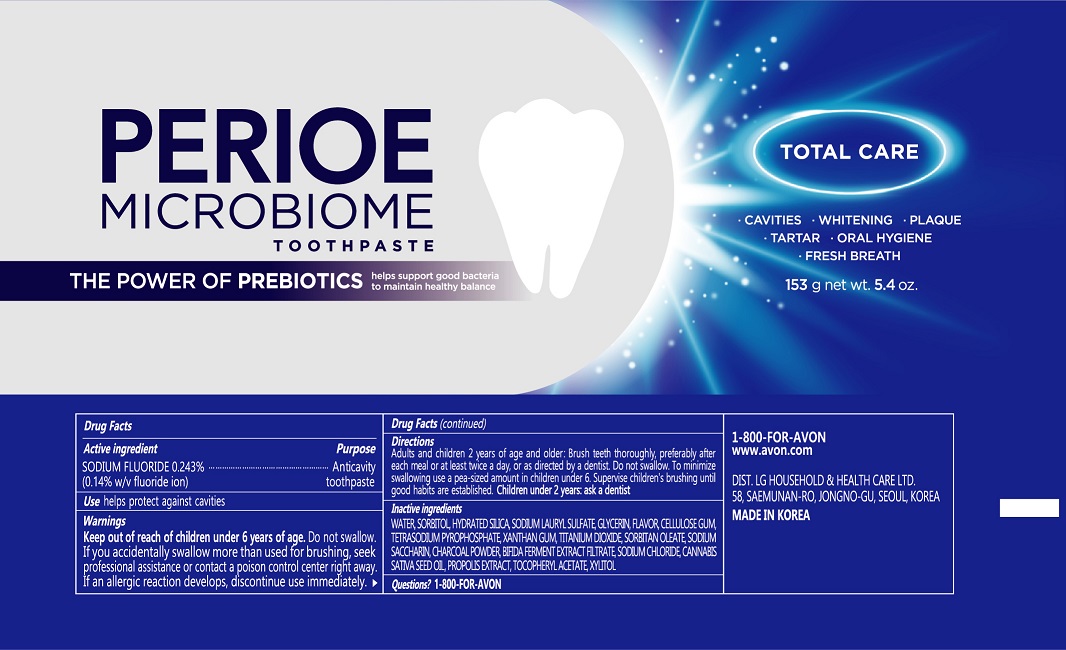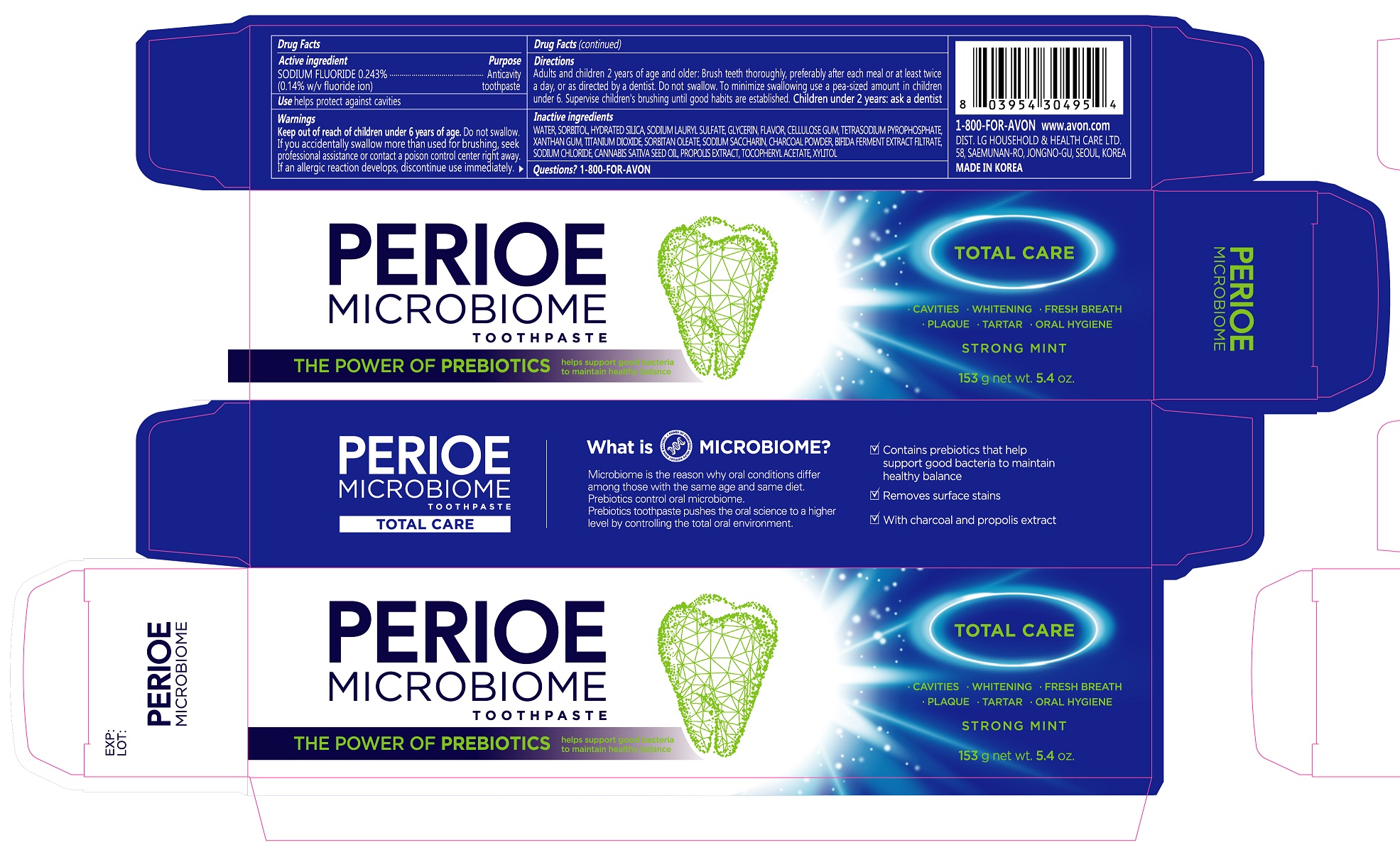 DRUG LABEL: PERIOE Microbiome Total Care
NDC: 43136-820 | Form: PASTE, DENTIFRICE
Manufacturer: Tai Guk Pharm. Co., Ltd.
Category: otc | Type: HUMAN OTC DRUG LABEL
Date: 20250101

ACTIVE INGREDIENTS: SODIUM FLUORIDE 1.4 mg/1 g
INACTIVE INGREDIENTS: HYDRATED SILICA; PROPOLIS WAX; GLYCERIN; WATER; SODIUM PYROPHOSPHATE; .ALPHA.-TOCOPHEROL ACETATE, DL-; SODIUM LAURYL SULFATE; XYLITOL; SACCHARIN SODIUM; CARBOXYMETHYLCELLULOSE SODIUM; TITANIUM DIOXIDE; CITRUS LIMON FRUIT OIL; SODIUM CHLORIDE; SORBITAN MONOOLEATE; XANTHAN GUM; MICA; ACTIVATED CHARCOAL; CANNABIS SATIVA SEED OIL

PERIOE Microbiome Total Care Toothpaste Strong Mint 153 g

Drug Facts

Active Ingredient

Sodium fluoride 0.243% (0.14% w/v fluoride ion)

Purpose

Anticavity toopaste

Use

helps protect against cavities

Warnings

Keep out of reach of children under 6 years of age.Do not swallow. If you accidentally swallow more than used for brushing, seek professional assistance or contact a poison control center right away. If an allergic reaction develops, discontinue use immediately.

Directions

Adults and children 2 years of age and and older: Brush teeth thoroughly, preferably after each meal or at least twice a day, or as directed by a dentist. Do not swallow. To minimize swallowing use a pea-sized amount in children under 6. Supervise children's brushing until good habits are established. Children under 2 years: ask a dentist.

Inactive Ingredients

WATER, SORBITOL, HYDRATED SILICA, SODIUM LAURYL SULFATE, GLYCERIN, FLAVOR, CELLULOSE GUM, TETRASODIUM PYROPHOSPHATE, XANTHAN GUM, TITANIUM DIOXIDE, SORBITAN OLEATE, SODIUM SACCHARIN, CHARCOAL POWDER, BIFIDA FERMENT EXTRACT FILTRATE, SODIUM CHLORIDE, CANNABIS SATINA SEED OIL, PROPOLIS EXTRACT, TOCOPHERYL ACETATE, XYLITOL

Questions?

1-800-FOR-AVON

Principal Display Panel - 153 g Tube Carton

PERIOE
MICROBIOME
TOOTHPASTE

THE POWER OF PREBIOTICS
helps support good bacteria
to maintain healthy balance

TOTAL CARE

- CAVITIES - WHITENING - PLAQUE
- TARTAR - ORAL HYGIENE
- FRESH BREATH
STRONG MINT

153 g net wt. 5.4 oz